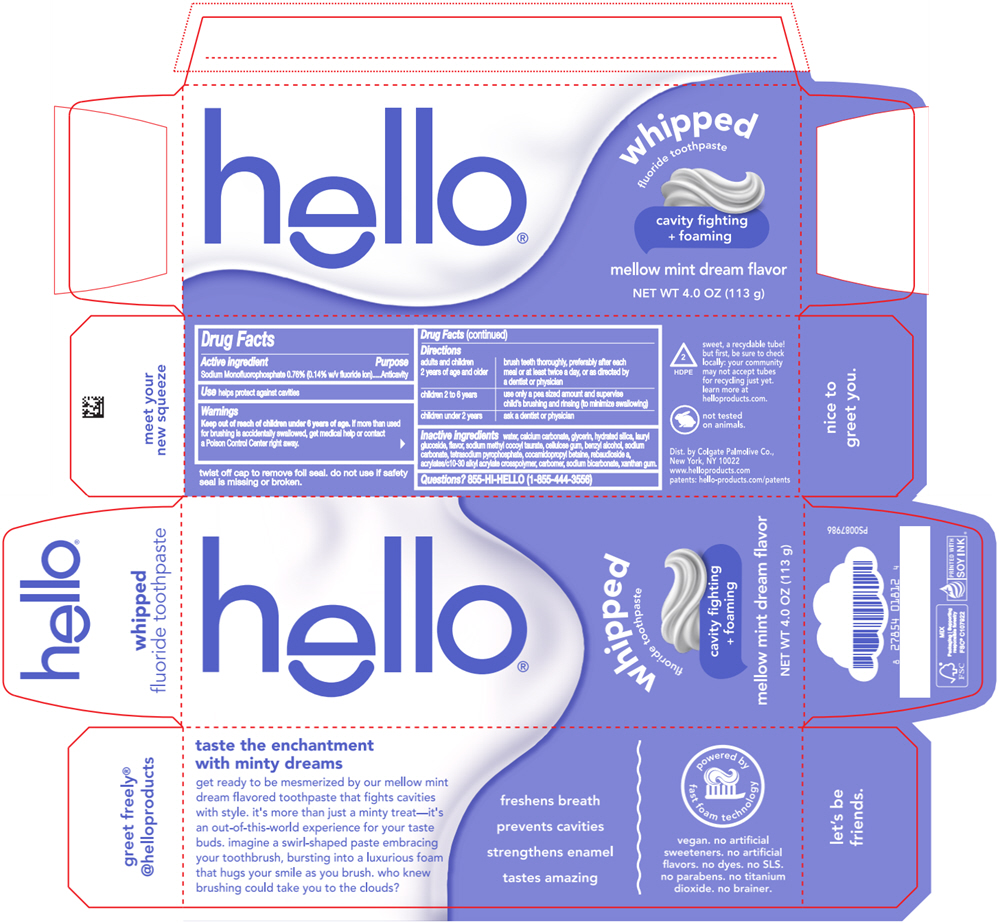 DRUG LABEL: Hello Whipped Mellow Mint Dream Flavor
NDC: 35000-513 | Form: PASTE, DENTIFRICE
Manufacturer: Colgate-Palmolive Company
Category: otc | Type: HUMAN OTC DRUG LABEL
Date: 20251111

ACTIVE INGREDIENTS: SODIUM MONOFLUOROPHOSPHATE 1.1 mg/1 g
INACTIVE INGREDIENTS: WATER; CALCIUM CARBONATE; GLYCERIN; HYDRATED SILICA; LAURYL GLUCOSIDE; SODIUM METHYL COCOYL TAURATE; CARBOXYMETHYLCELLULOSE SODIUM, UNSPECIFIED; BENZYL ALCOHOL; SODIUM CARBONATE; SODIUM PYROPHOSPHATE; COCAMIDOPROPYL BETAINE; REBAUDIOSIDE A; ACRYLATES/C10-30 ALKYL ACRYLATE CROSSPOLYMER (60000 MPA.S); CARBOMER HOMOPOLYMER, UNSPECIFIED TYPE; SODIUM BICARBONATE; XANTHAN GUM

Hello® Whipped Mellow Mint Dream Flavor

Drug Facts

Active ingredient

Sodium Monofluorophosphate 0.76% (0.14% w/v fluoride ion)

Purpose

Anticavity

Use

helps protect against cavities

Warnings

Keep out of reach of children under 6 years of age. If more than used for brushing is accidentally swallowed, get medical help or contact a Poison Control Center right away.

Directions

adults and children 2 years of age and older | brush teeth thoroughly, preferably after each meal or at least twice a day, or as directed by a dentist or physician
children 2 to 6 years | use only a pea sized amount and supervise child's brushing and rinsing (to minimize swallowing)
children under 2 years | ask a dentist or physician

Inactive ingredients

water, calcium carbonate, glycerin, hydrated silica, lauryl glucoside, sodium methyl cocoyl taurate, cellulose gum, benzyl alcohol, sodium carbonate, tetrasodium pyrophosphate, cocamidopropyl betaine, rebaudioside a, acrylates/c10-30 alkyl acrylate crosspolymer, carbomer, sodium bicarbonate, xanthan gum.

Questions?

855-HI-HELLO (1-855-444-3556)

Dist. by Colgate Palmolive Co.,
New York, NY 10022

PRINCIPAL DISPLAY PANEL - 113 g Tube Carton

hello®

whipped
fluoride toothpaste

cavity fighting
+ foaming

mellow mint dream flavor

NET WT 4.0 OZ (113 g)